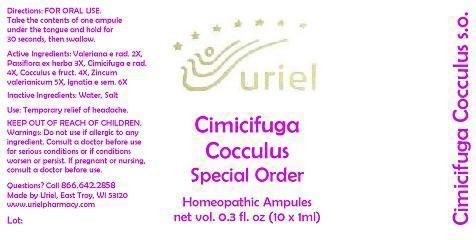 DRUG LABEL: Cimicifuga Cocculus Special Order
NDC: 48951-3198 | Form: LIQUID
Manufacturer: Uriel Pharmacy Inc.
Category: homeopathic | Type: HUMAN OTC DRUG LABEL
Date: 20150227

ACTIVE INGREDIENTS: VALERIAN 2 [hp_X]/1 mL; PASSIFLORA INCARNATA FLOWERING TOP 3 [hp_X]/1 mL; BLACK COHOSH 4 [hp_X]/1 mL; ANAMIRTA COCCULUS WHOLE 4 [hp_X]/1 mL; ZINC 5 [hp_X]/1 mL; STRYCHNOS IGNATII SEED 6 [hp_X]/1 mL
INACTIVE INGREDIENTS: WATER; SODIUM CHLORIDE

Cimicifuga Cocculus Special Order

INDICATIONS AND USAGE

Directions: FOR ORAL USE.

DOSAGE AND ADMINISTRATION

Take the contents of one ampule under the tongue and hold for 30 seconds, then swallow.

ACTIVE INGREDIENT

Active Ingredients: Valeriana e rad. 2X, Passiflora ex herba 3X, Cimicifuga e rad. 4X, Cocculus e fruct. 4X, Zincum valerianicum 5X, Ignatia e sem. 6X

Inactive Ingredients: Water, Salt

PURPOSE

Use: Temporary relief of headache.

KEEP OUT OF REACH OF CHILDREN.

WARNINGS

Warnings: Do not use if allergic to any ingredient. Consult a doctor before use for serious conditions or if conditions worsen or persist. If pregnant or nursing, consult a doctor before use.

QUESTIONS

Questions? Call 866.642.2858 Made by Uriel, East Troy, WI 53120 www.urielpharmacy.com